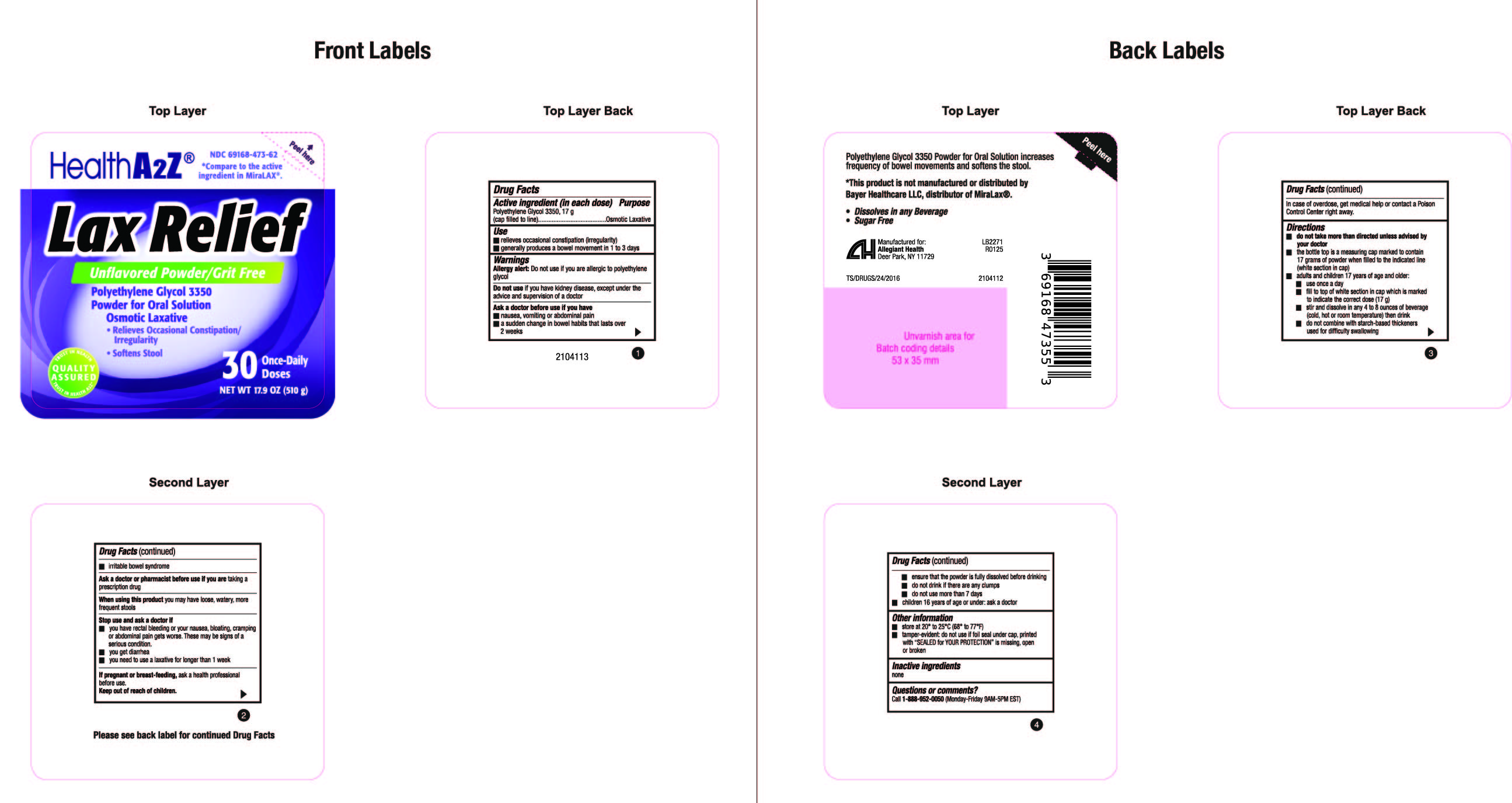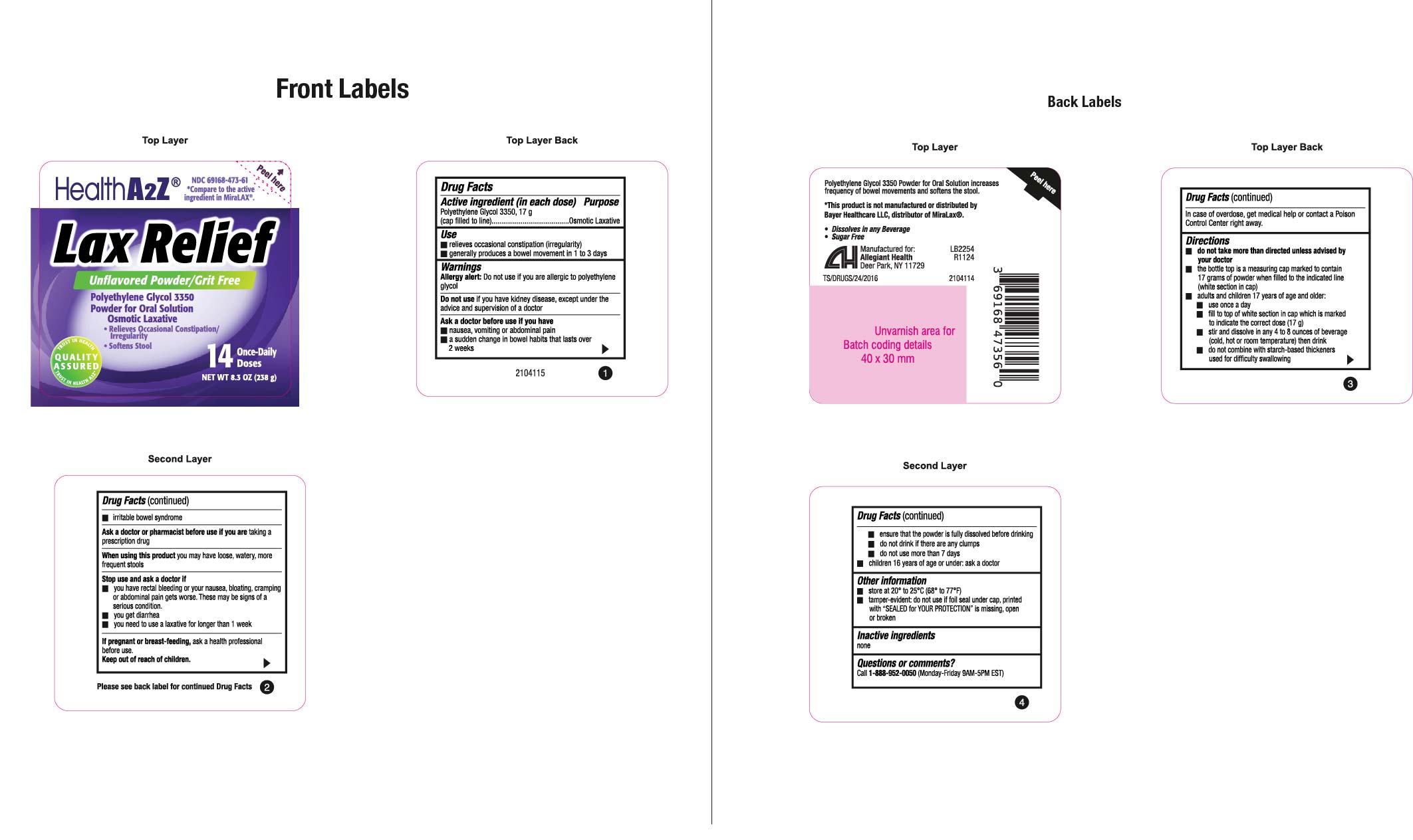 DRUG LABEL: Polyethylene Gycol 3350
NDC: 69168-473 | Form: POWDER, FOR SOLUTION
Manufacturer: Allegiant Health
Category: otc | Type: HUMAN OTC DRUG LABEL
Date: 20250317

ACTIVE INGREDIENTS: POLYETHYLENE GLYCOL 3350 17 g/1 g

473 - PEG 3350 Powder

Active ingredient(s)

Polyethylene Glycol 3350, 17 g (cap filled to line)

Purpose

Osmotic Laxative

Use(s)

- relieves occasional constipation (irregularity)
- generally produces a bowel movement in 1 to 3 days

Warnings

Allergy alert: Do not use if you are allergic to polyethylene glycol.

Do not use

if you have kidney disease, except under the advice and supervision of a doctor

Ask a doctor before use if

- nausea, vomiting or abdominal pain
- a sudden change in bowel habits that lasts over 2 weeks
- irritable bowel syndrome

Ask a doctor or pharmacist before use if

you are taking a prescription drug

When using this product

you may have loose, watery, more frequent stools

Stop use and ask a doctor if

- you have rectal bleeding or your nausea, bloating, cramping or
  abdominal pain gets worse. These may be signs of a serious condition.
- you get diarrhea
- you need to use a laxative for longer than 1 week

If pregnant or breastfeeding,

ask a health professional before use.

Keep out of reach of children

In case of overdose, get medical help or contact a Poison Control Center (1-800-222-1222) right away.

Directions

do not take more than directed unless advised by your doctor
• the bottle top is a measuring cap marked to contain 17 grams of powder when filled to the indicated line (white section in cap)

• adults and children 17 years of age and older:

• use once a day
• fill to top of white section in cap which is marked to indicate the correct dose (17 g)
• stir and dissolve in any 4 to 8 ounces of beverage (cold, hot or room temperature) then drink

• do not combine with starch-based thickeners used for difficult swallowing
• ensure that the powder is fully dissolved before drinking
• do not drink if there are any clumps
• do not use more than 7 days
• children 16 years of age or under: ask a doctor

Other information

- store at 20° to 25°C (68° to 77°F)
- tamper-evident: do not use if foil seal under cap, printed
  with “SEALED for YOUR PROTECTION” is missing, open
  or broken

Inactive ingredients

None

Questions/Comments

Call 1-888-952-0050 Monday through Friday 9AM - 5PM EST

Principal Display Panel

PEG 3350 Powder 510g
PEG 3350 Powder 238g